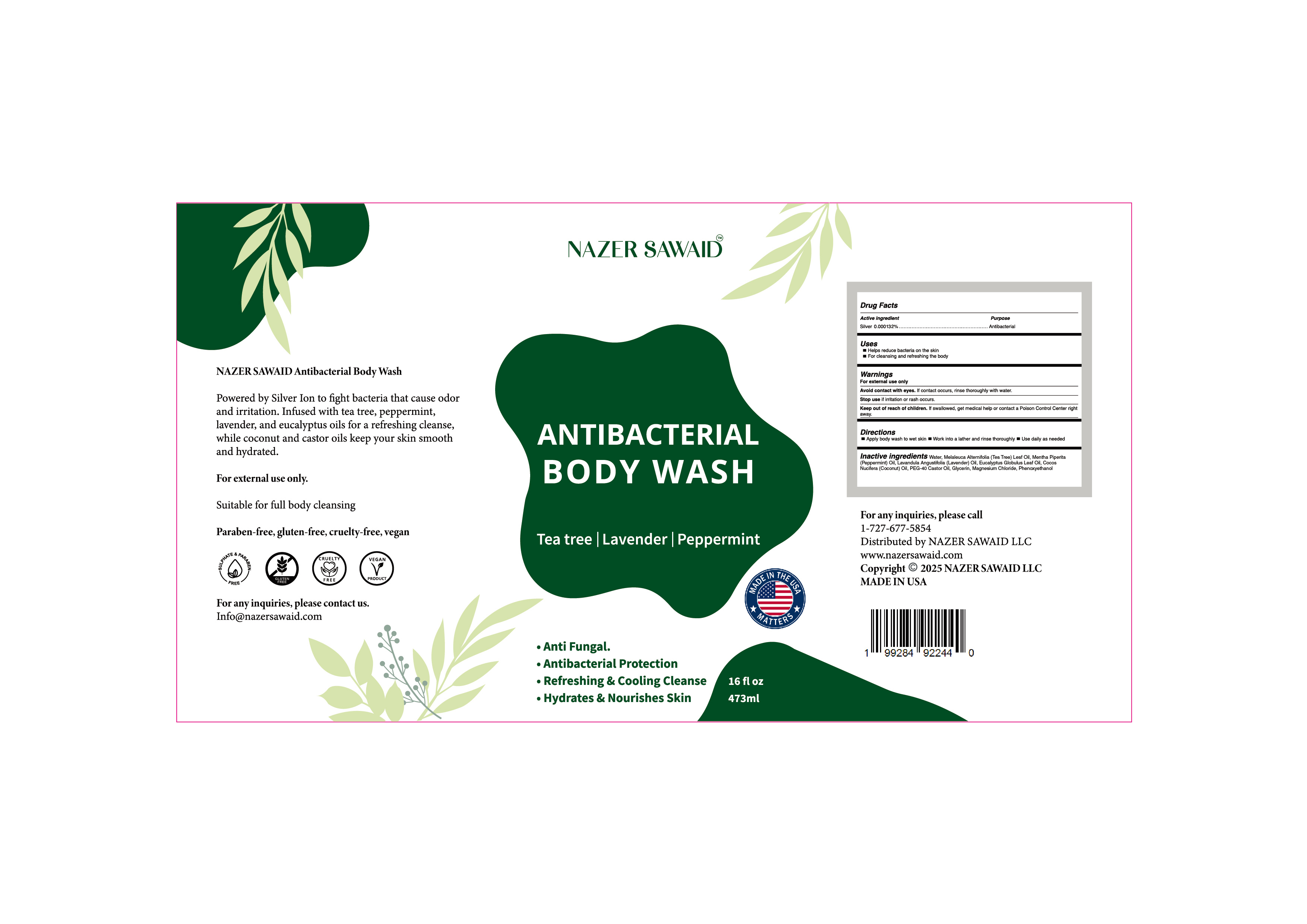 DRUG LABEL: antibacterial body wash
NDC: 85434-003 | Form: LIQUID
Manufacturer: Guangdong Quaker Daily Chemical Co., LTD
Category: otc | Type: HUMAN OTC DRUG LABEL
Date: 20250930

ACTIVE INGREDIENTS: SILVER 0.000132 g/100 mL
INACTIVE INGREDIENTS: COCOS NUCIFERA (COCONUT) OIL; PEG-40 CASTOR OIL; GLYCERIN; WATER; MENTHA PIPERITA (PEPPERMINT) OIL; PHENOXYETHANOL; MELALEUCA ALTERNIFOLIA (TEA TREE) LEAF OIL; EUCALYPTUS GLOBULUS LEAF OIL; LAVANDULA ANGUSTIFOLIA (LAVENDER) OIL; MAGNESIUM CHLORIDE

85434-003 antibacterial body wash

ACTIVE INGREDIENT

Silver 0.000132%

PURPOSE

Antibacterial

INDICATIONS AND USAGE

Helps reduce bacteria on the skin

For cleansing and refreshing the body

WARNINGS

For external use only

WHEN USING

Avoid contact with eyes. lf contact occurs, rinse thoroughly with water.

Stop use if irritation or rash occurs.

Keep out of reach of children. lf swallowed, get medical help or contact a Poison Control Center right away.

DOSAGE AND ADMINISTRATION

Apply body wash to wet skin
Work into a lather and rinse thorouahly
Use aaily as needed

INACTIVE INGREDIENT

MELALEUCA ALTERNIFOLIA (TEA TREE) LEAF OIL
MENTHA PIPERITA (PEPPERMINT) OIL
LAVANDULA ANGUSTIFOLIA (LAVENDER) OIL
EUCALYPTUS GLOBULUS LEAF OIL
COCOS NUCIFERA (COCONUT) OIL
PEG-40 CASTOR OIL
GLYCERIN
MAGNESIUM CHLORIDE
PHENOXYETHANOL